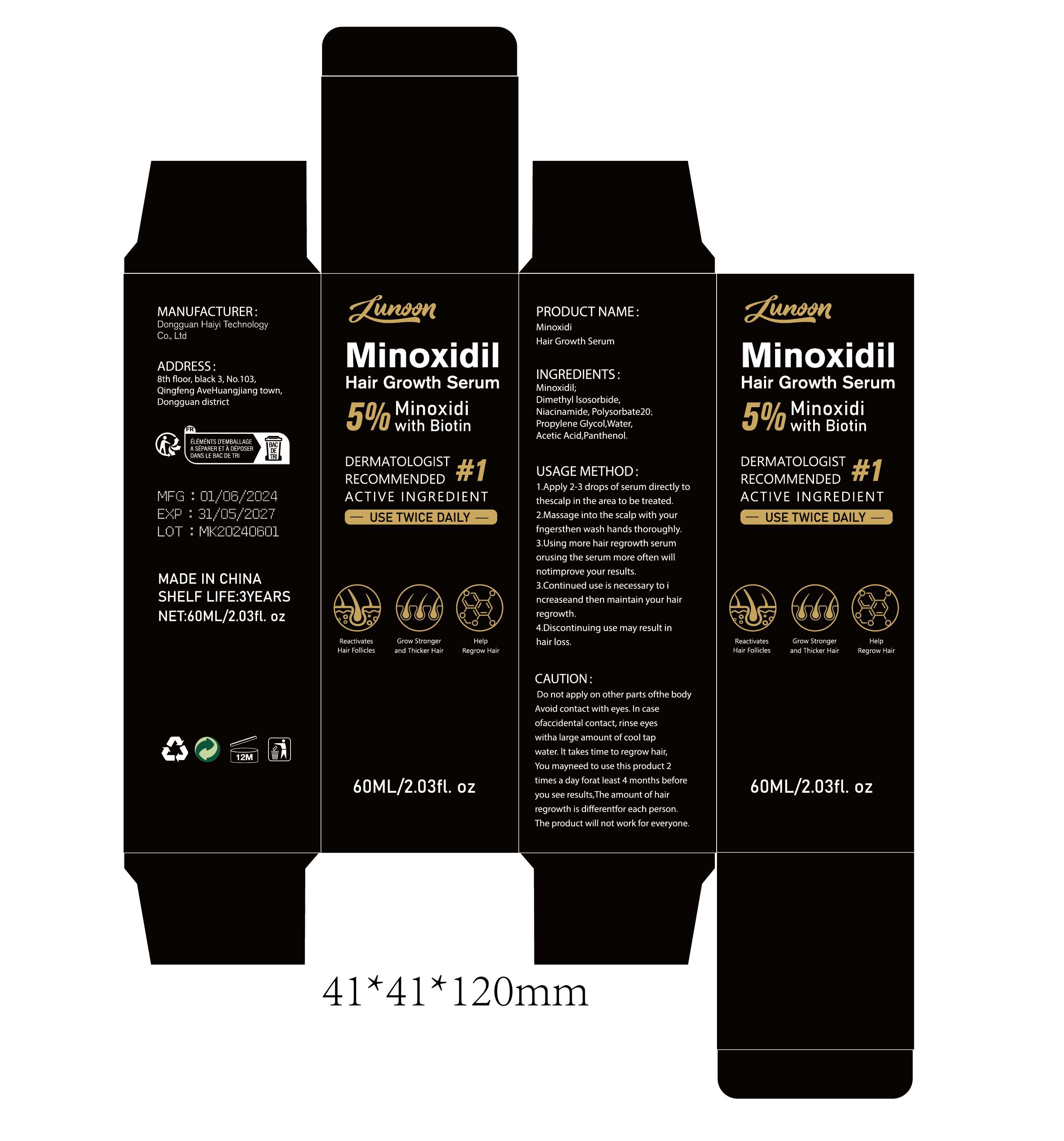 DRUG LABEL: Minoxidi Hair Growth Serum
NDC: 84732-014 | Form: CREAM
Manufacturer: Dongguan Haiyi Technology Co.,Ltd.
Category: otc | Type: HUMAN OTC DRUG LABEL
Date: 20240925

ACTIVE INGREDIENTS: MINOXIDIL 1 mg/60 mL
INACTIVE INGREDIENTS: NIACINAMIDE; POLYSORBATE 20; WATER; ACETIC ACID; PANTHENOL; DIMETHYL ISOSORBIDE; PROPYLENE GLYCOL

Active ingredient

Minoxidil;

Inactive ingredient

Dimethyl Isosorbide
Niacinamide,Polysorbate 20:
Propylene Glycol，Water,
Acetic Acid,Panthenol.

Purpose section

1.Reactivates Hair Follicles
2.Grow Stronger and Thicker Hair

3.Help Regrow Hair

Warning

Do not apply on other parts ofthe body Avoid contact with eyes. In case ofaccidental contact, rinse eyes witha large amount of cool tap water.

stop use

This product may cause allergic reactions in asmall number of people.
lf youexperience any discomfort,please stop using it immediately.

not use

Not suitable for use by children, pregnantor breast feeding people.

OUT OF CHILDREN

KEEP THE PRODUCT OUT OF REACH OF CHILDREN to

HOW TO USE

1.Apply 2-3 drops of serum directly tothescalp in the area to be treated.

2.Massage into the scalp with yourfngersthen wash hands thoroughly.

3.Using more hair regrowth serumorusing the serum more often willnotimprove your results.

4.Continued use is necessary to increaseand then maintain your hair regrowth.
5.Discontinuing use may result inhair loss.

Dosage

lt takes time to regrow hairYou mayneed to use this product 2times a day forat least 4 months beforeyou see results,The amount of hair regrowth is different for each person.The product will not work for everyone.